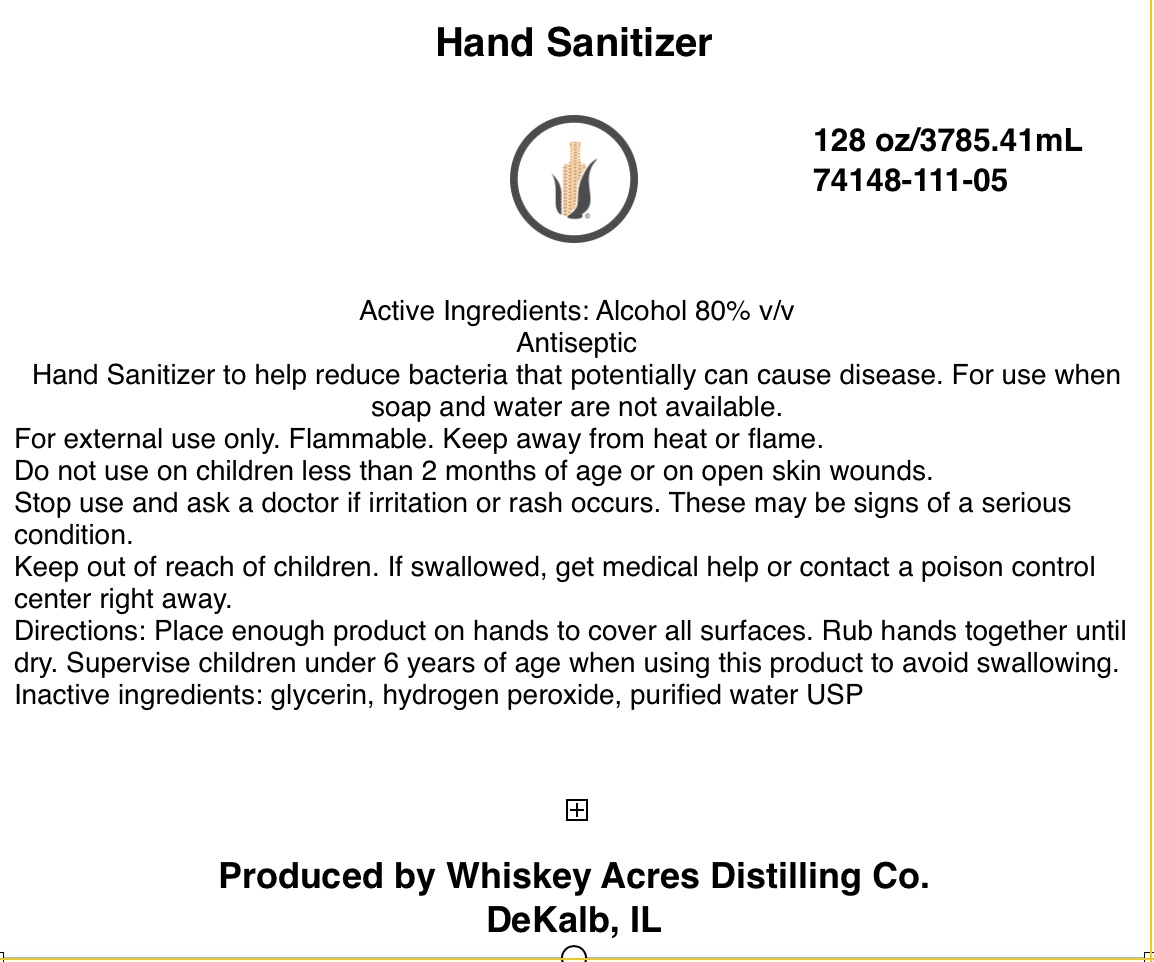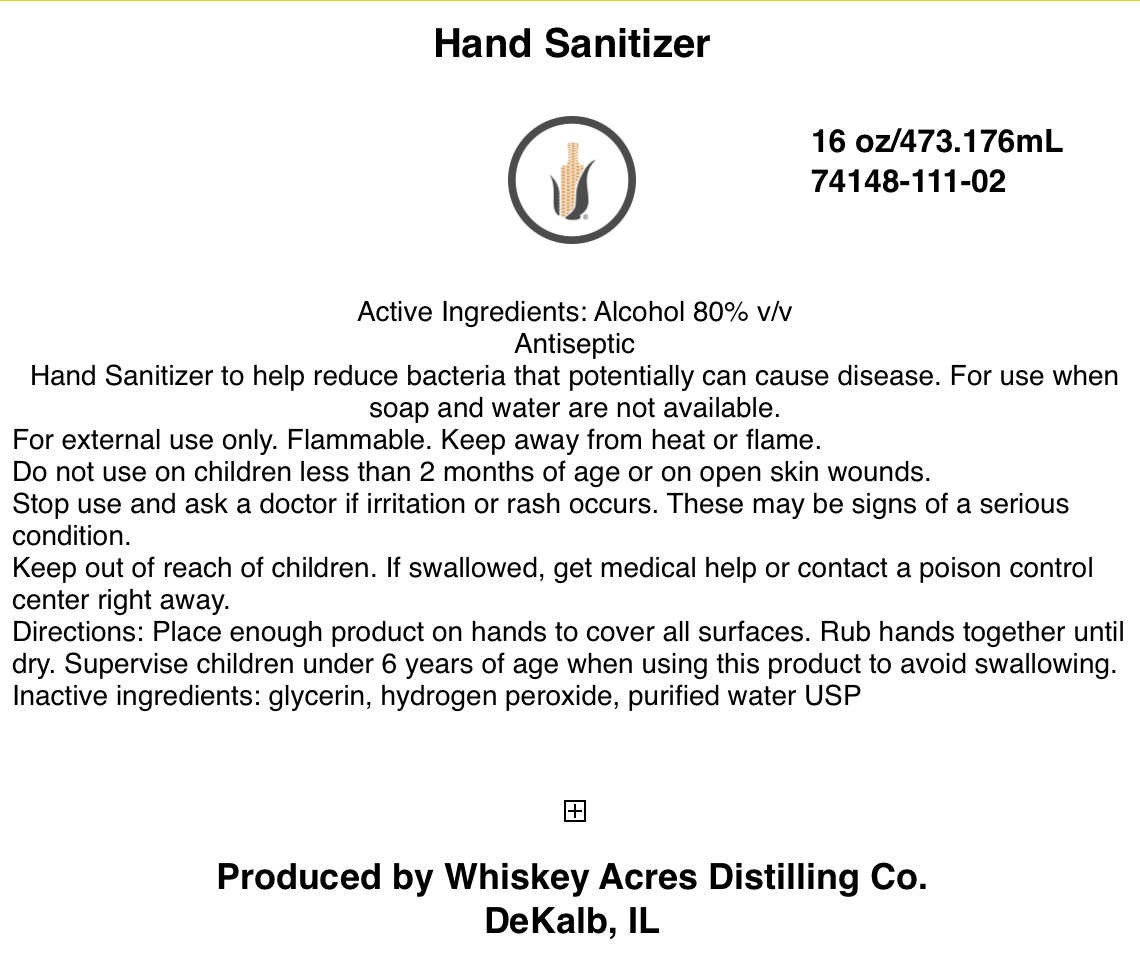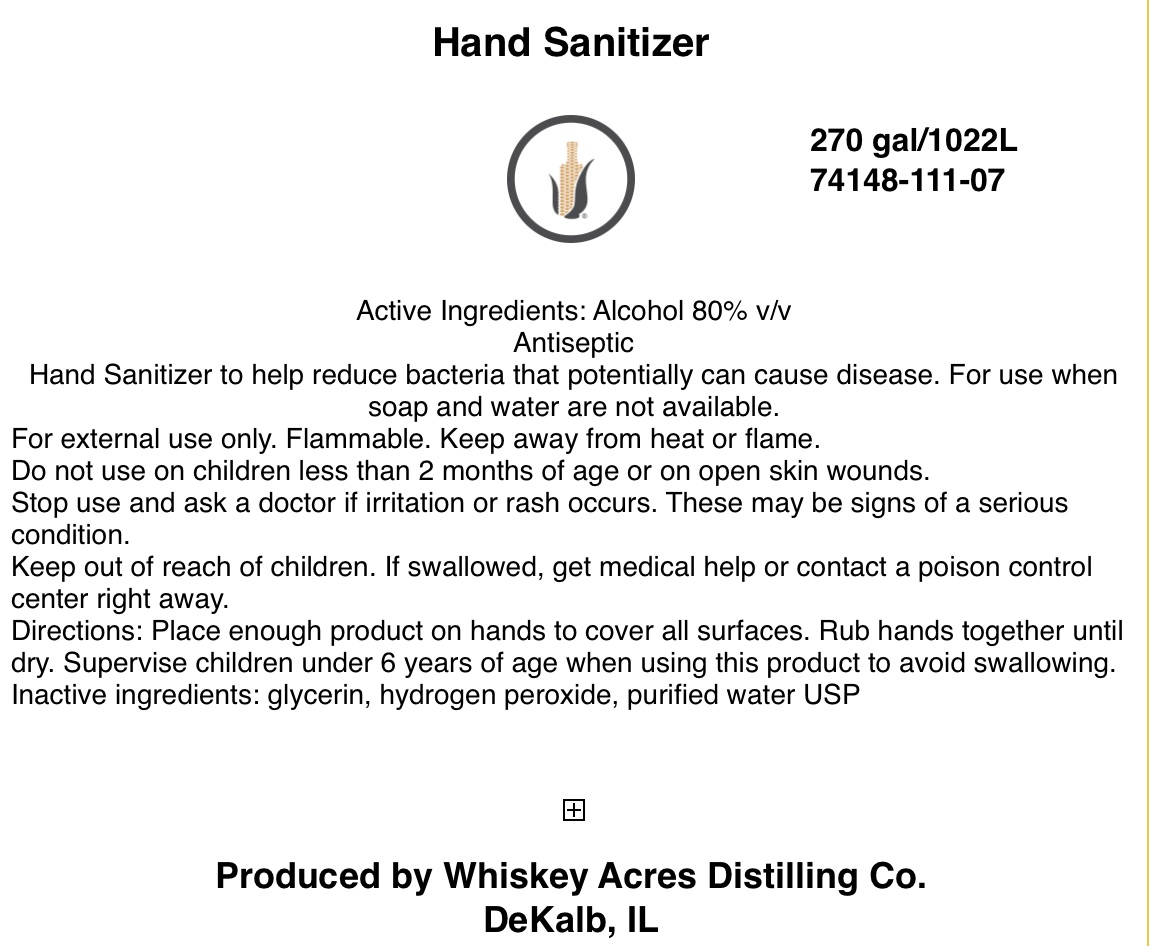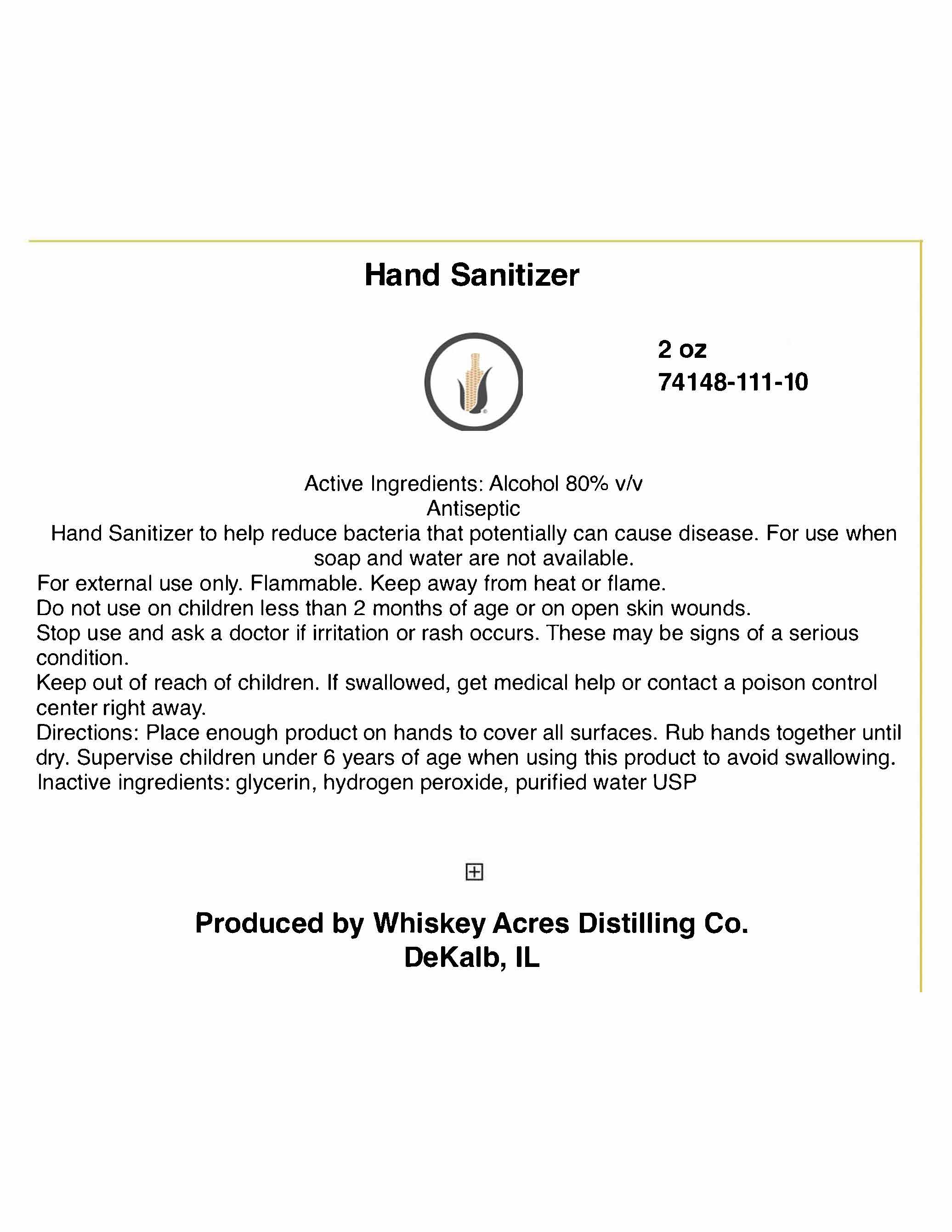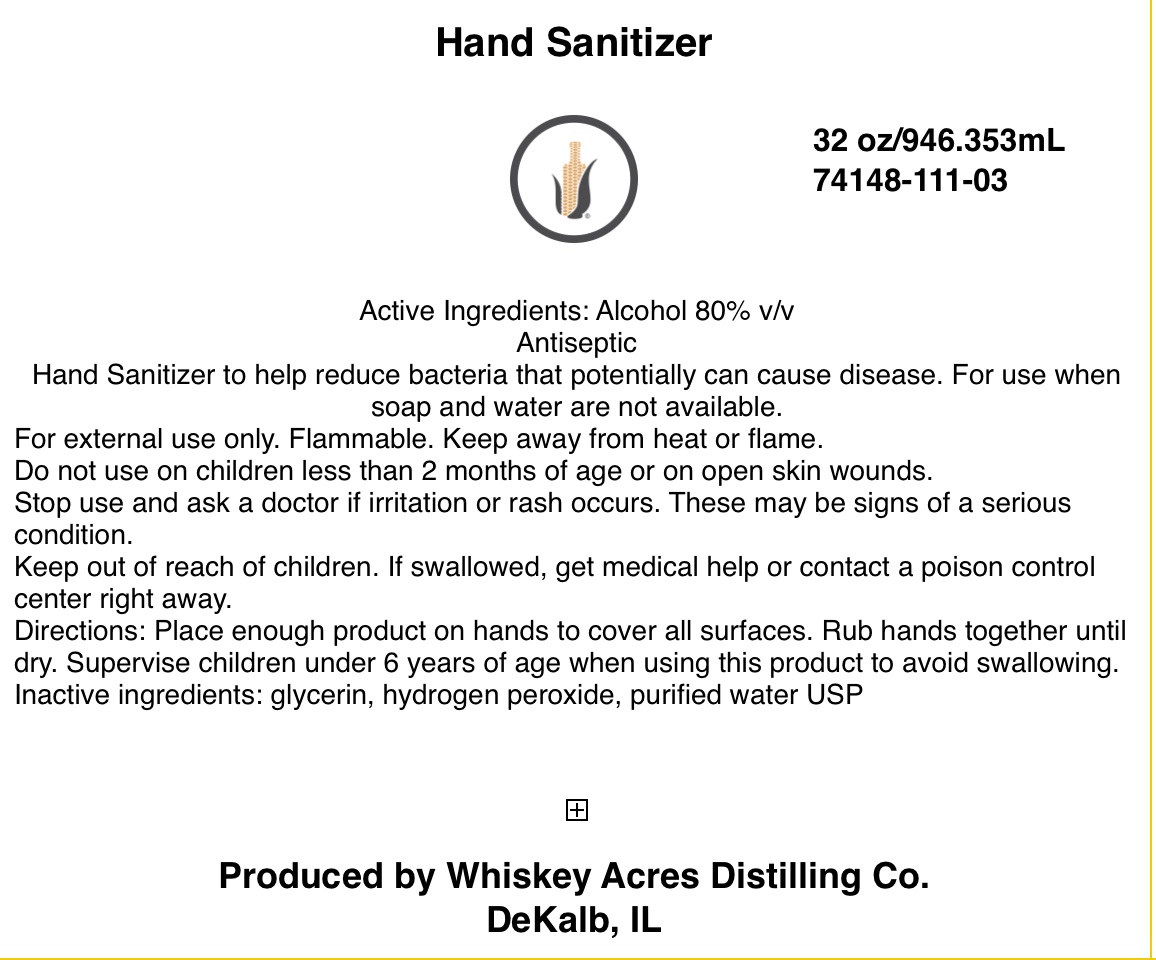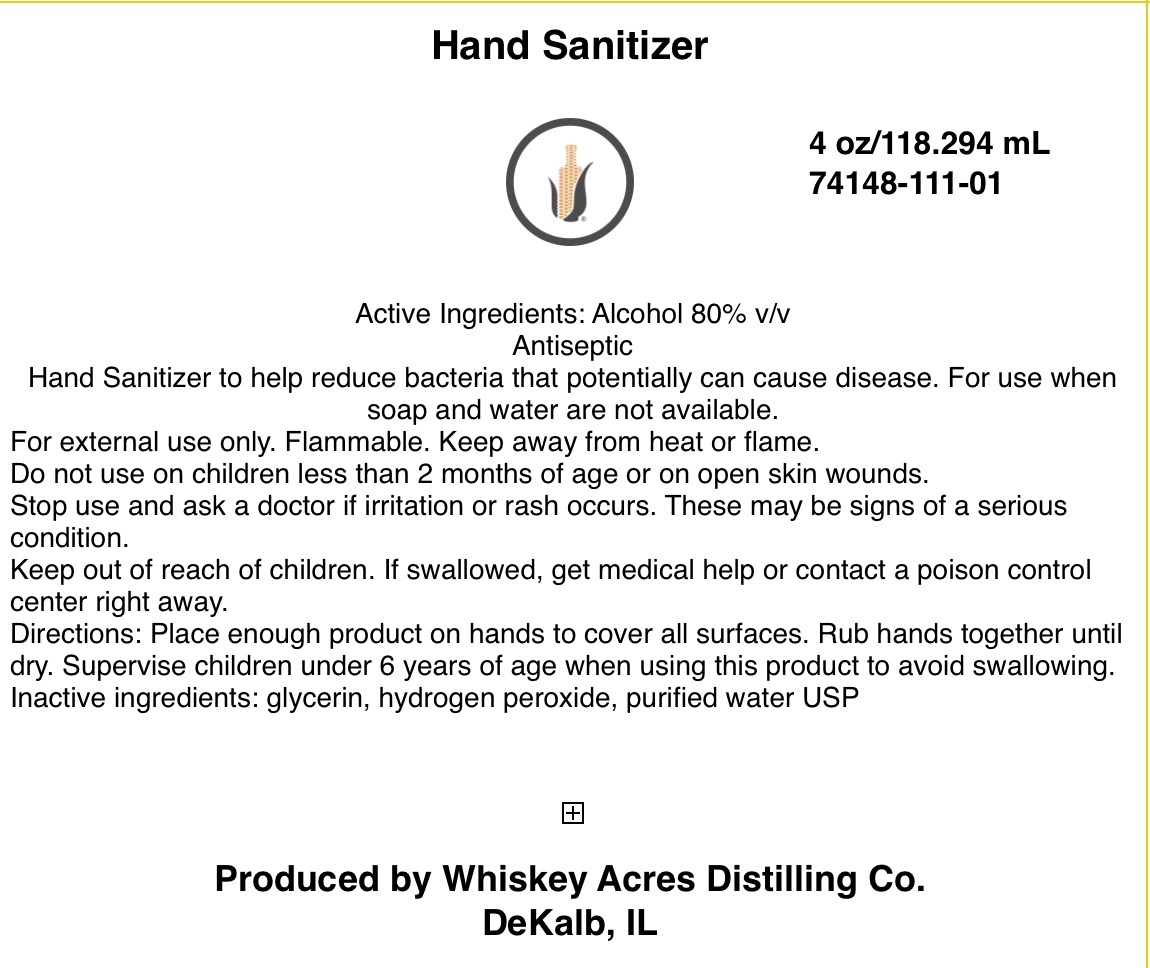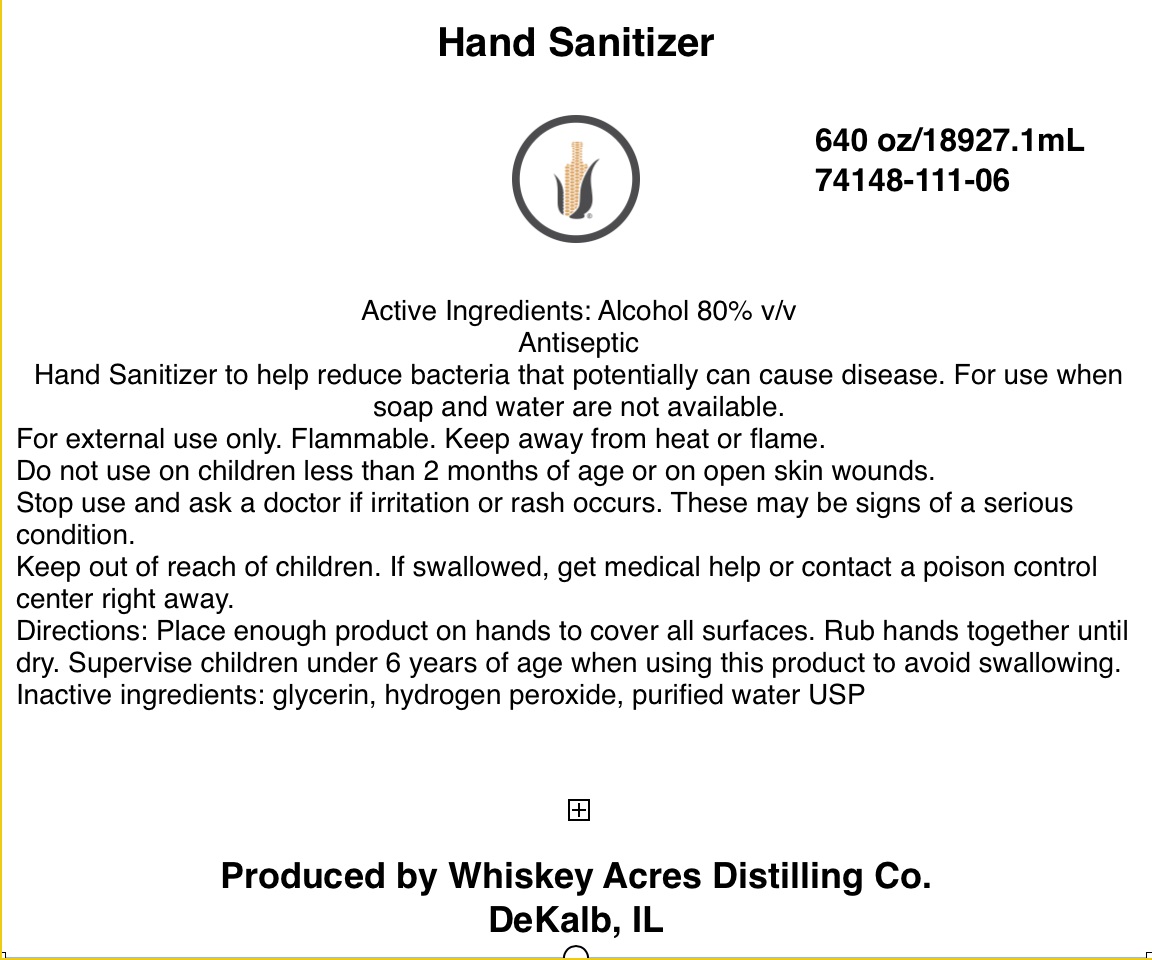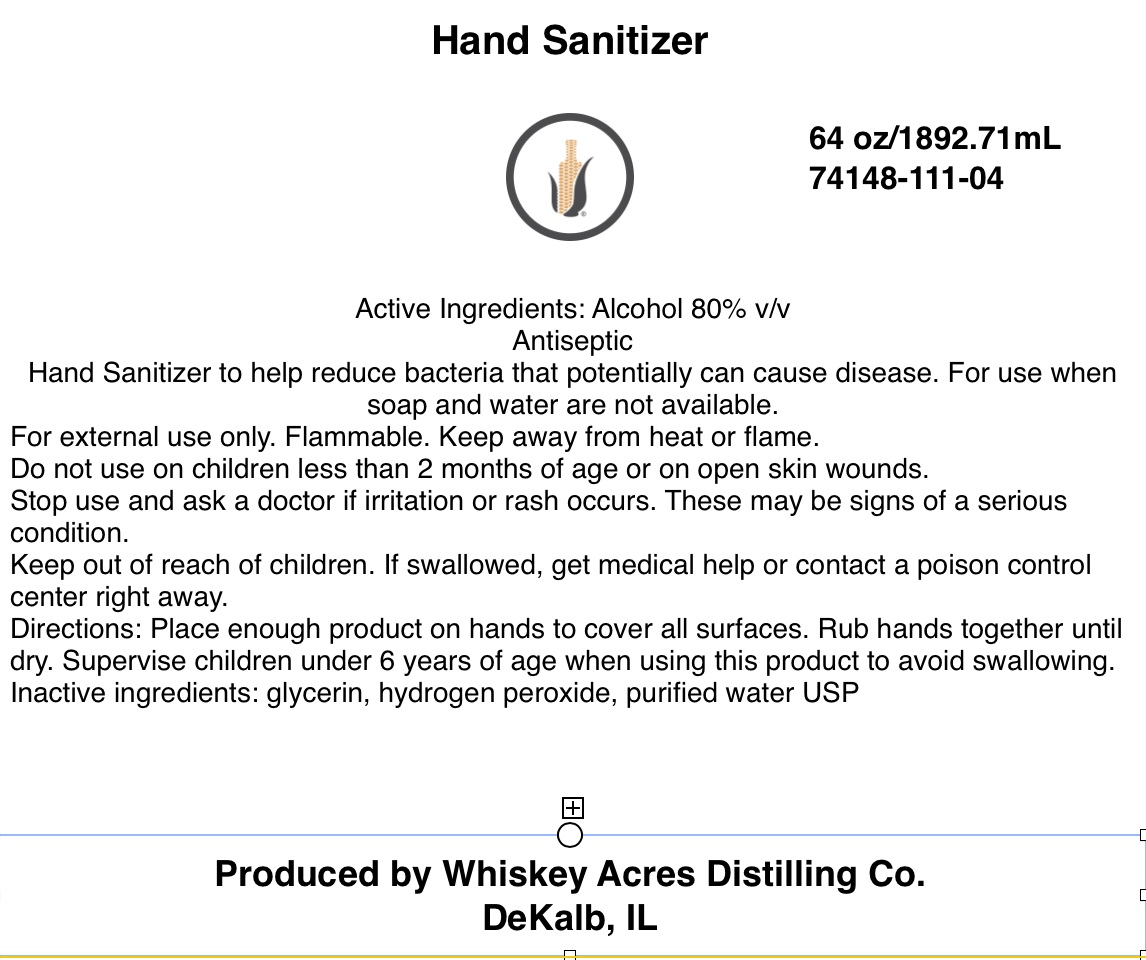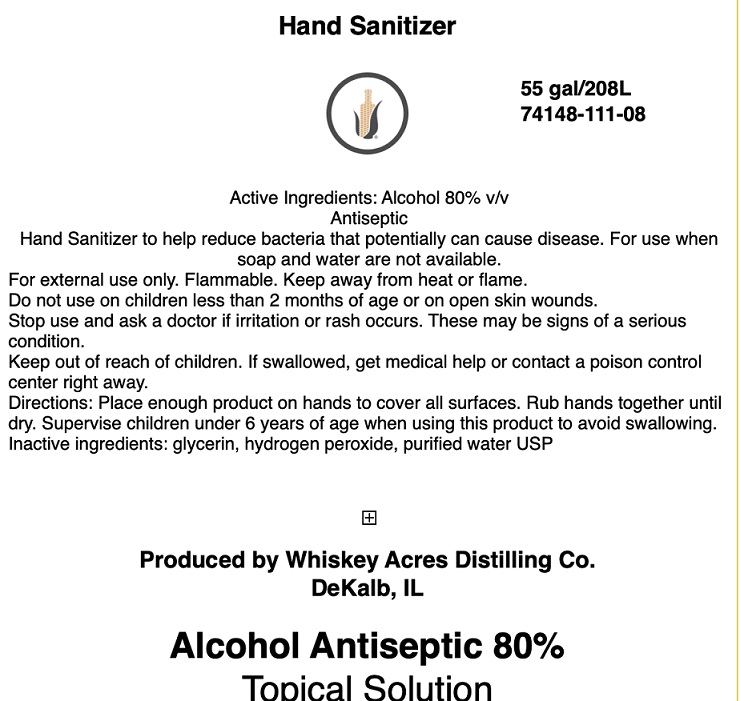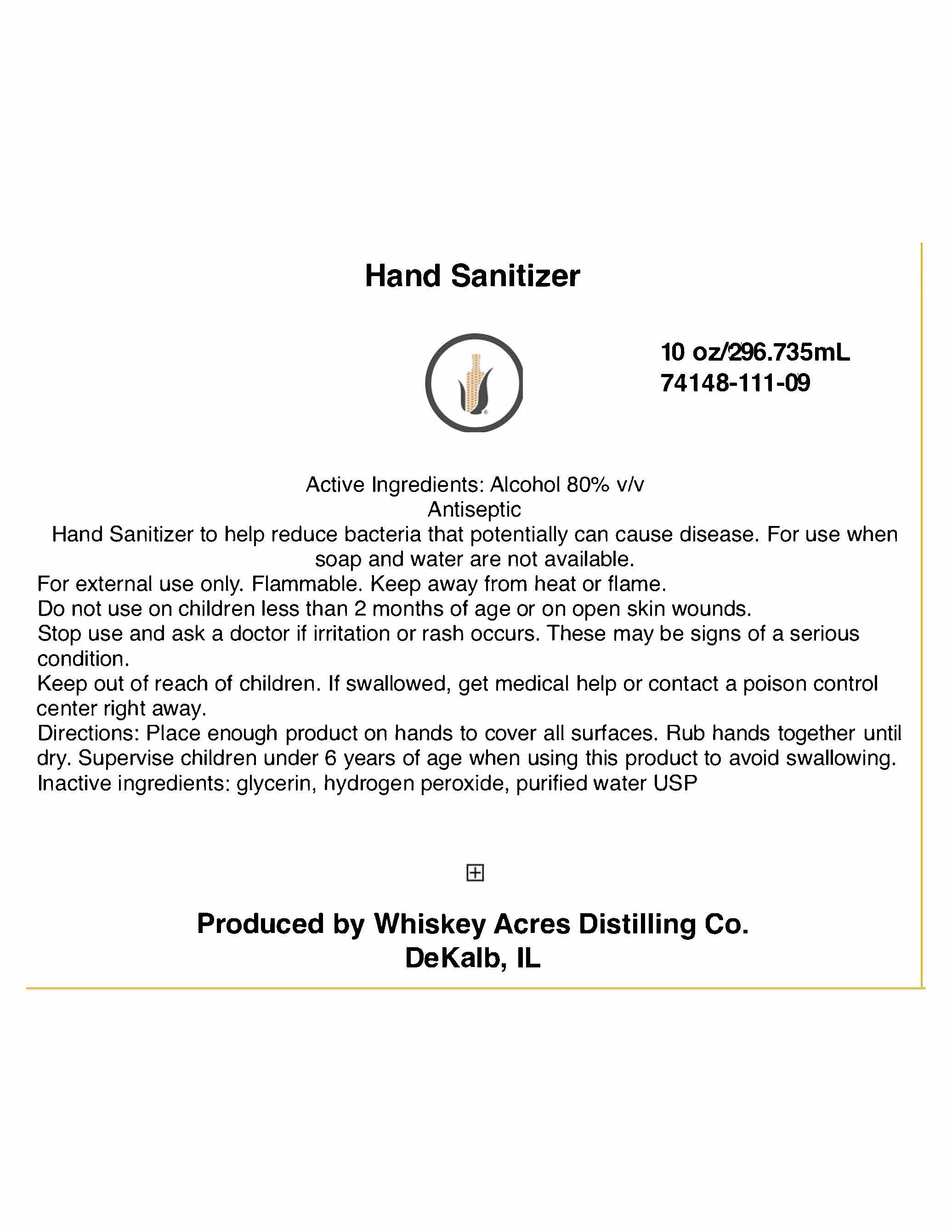 DRUG LABEL: Hand Sanitizer
NDC: 74148-111 | Form: LIQUID
Manufacturer: Whiskey Acres Distilling Company
Category: otc | Type: HUMAN OTC DRUG LABEL
Date: 20200811

ACTIVE INGREDIENTS: ALCOHOL 80 mL/100 mL
INACTIVE INGREDIENTS: GLYCERIN; HYDROGEN PEROXIDE; WATER

Hand sanitizer

ACTIVE INGREDIENT

Alcohol 80 % v/v

PURPOSE

Antiseptic

INDICATIONS AND USAGE

Hand Sanitizer to help reduce bacteria that potentially can cause disease. For use when soap and water are not available.

WARNINGS

For external use only. Flammable. Keep away from heat or flame

DO NOT USE

- In children less than 2 months of age
- On open skin wounds

Stop use and ask a doctor if irritation or rash occurs. These may be signs of a serious condition.

Keep out of reach of children. If swallowed, get medical help or contact a poison control center right away.

Directions:

- Place enough product on hands to cover all surfaces. Rub hands together until dry.
- Supervise children under 6 years of age when using this product to avoid swallowing.

Other Information:

Store between 15-30c (59-86F)

Avoid freezing and excessive heat above 40 C (104F)

Inactive ingredients glycerin, hydrogen peroxide, purified water USP